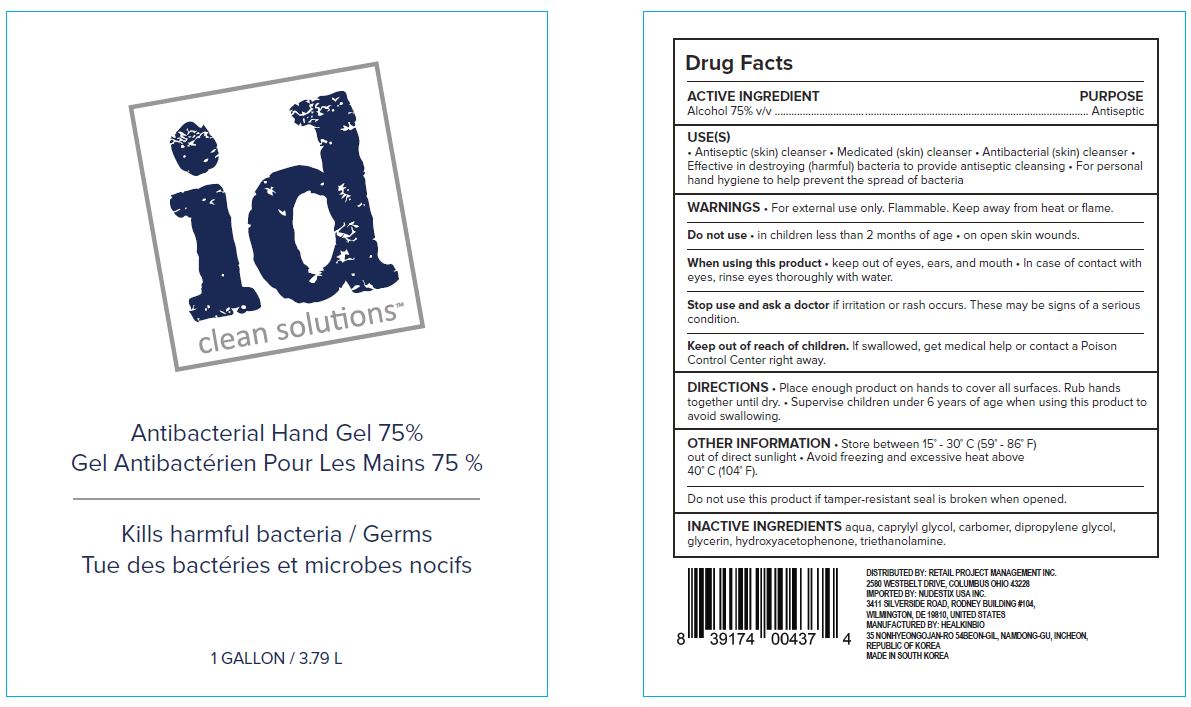 DRUG LABEL: Innovate Hand Sanitizer
NDC: 76586-113 | Form: GEL
Manufacturer: HEALKINBIO CO.
Category: otc | Type: HUMAN OTC DRUG LABEL
Date: 20200804

ACTIVE INGREDIENTS: ALCOHOL 75 mL/100 mL
INACTIVE INGREDIENTS: CAPRYLYL GLYCOL; WATER; TROLAMINE; DIPROPYLENE GLYCOL; GLYCERIN; HYDROXYACETOPHENONE; CARBOMER 940

Active Ingredient(s)

alcohol

Purpose

Purpose: Antiseptic

Use

 Hand sanitizing to help reduce bacteria on the skin

Warnings

 For external use only.
 Flammable, keep away from fire or flame.
 When using this product, avoid contact with the eyes. In case of contact, rinse eyes thoroughly with water.
 Stop use and ask a doctor if irritation or redness appears and lasts.

 Keep out of reach of children. If swallowed, get medical help or contact a Poison Control Center immediately.

Directions

 Take suitable amount of sanitizer in the hand. Wet thoroughly and rub hands together until dry

INACTIVE INGREDIENT

aqua, caprylyl glycol, carbomer, dipropylene glycol, glycerin, hydroxyacetophenone, triethanolamine